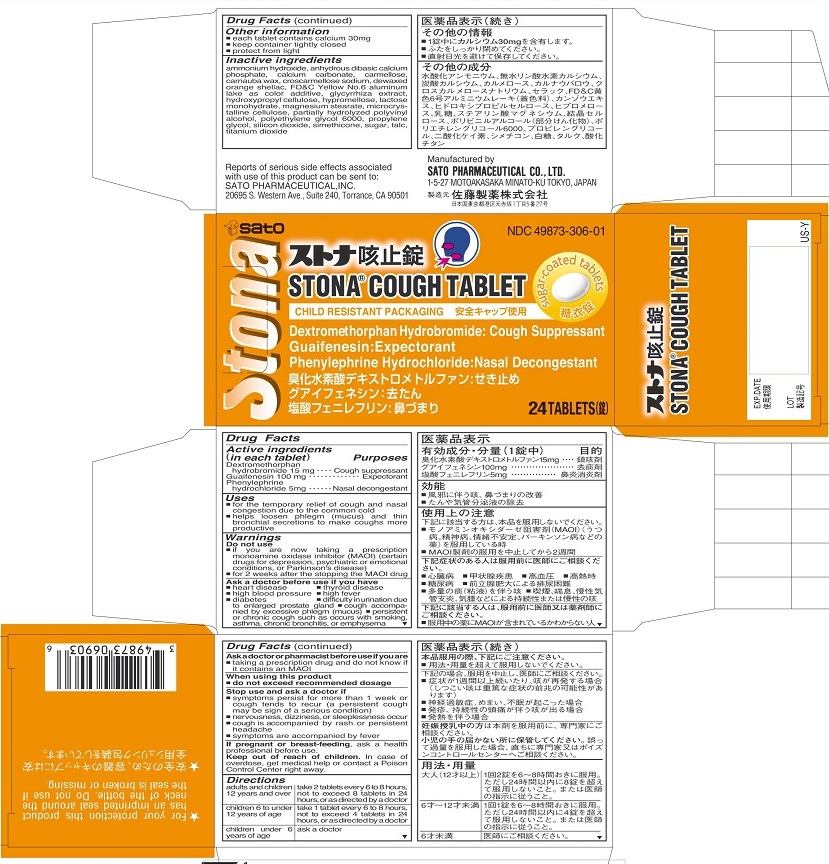 DRUG LABEL: Stona Cough
NDC: 49873-306 | Form: TABLET
Manufacturer: Sato Pharmaceutical Co., Ltd.
Category: otc | Type: HUMAN OTC DRUG LABEL
Date: 20231204

ACTIVE INGREDIENTS: DEXTROMETHORPHAN HYDROBROMIDE 15 mg/1 1; GUAIFENESIN 100 mg/1 1; PHENYLEPHRINE HYDROCHLORIDE 5 mg/1 1
INACTIVE INGREDIENTS: AMMONIA; CALCIUM CARBONATE; CARBOXYMETHYLCELLULOSE; CARNAUBA WAX; CROSCARMELLOSE SODIUM; SHELLAC; CALCIUM PHOSPHATE, DIBASIC, ANHYDROUS; FD&C YELLOW NO. 6; ALUMINUM OXIDE; LICORICE; HYDROXYPROPYL CELLULOSE; HYPROMELLOSES; LACTOSE MONOHYDRATE; MAGNESIUM STEARATE; CELLULOSE, MICROCRYSTALLINE; POLYVINYL ALCOHOL; POLYETHYLENE GLYCOL 6000; PROPYLENE GLYCOL; SILICON DIOXIDE; DIMETHICONE; SUCROSE; TALC; TITANIUM DIOXIDE

Stona Cough Tablet

Active ingredients (in each tablet)
Dextromethorphan hydrobromide 15mg
Guaifenesin 100 mg
Phenylephrine hydrochloride 5 mg

Purposes
Dextromethorphan hydrobromide Cough suppressant

Guaifenesin Expectorant
Phenylephrine hydrochloride Nasal decongestant

Uses
■ for the temporary relief of cough and nasal congestion due to the common cold
■ helps loosen phlegm (mucus) and thin bronchial secretions to make coughs more productive

Warnings

Do not use
■ if you are now taking a prescription monoamine oxidase inhibitor (MAOI) (certain drugs for depression, psychiatric or emotional conditions, or Parkinson’s disease)
■ for 2 weeks after the stopping the MAOI drug

Ask a doctor before use if you have
■ heart disease ■ thyroid disease
■ high blood pressure ■ high fever ■ diabetes
■ difficulty in urination due to enlarged prostate gland
■ cough accompanied by excessive phlegm (mucus)
■ persistent or chronic cough such as occurs with smoking, asthma, chronic bronchitis, or emphysema

Ask a doctor or pharmacist before use if you are
■ taking a prescription drug and do not know if it contains an MAOI

When using this product
■ do not exceed recommended dosage

Stop use and ask a doctor if
■ symptoms persist for more than 1 week or cough tends to recur (a persistent cough may be sign of a serious condition)
■ nervousness, dizziness, or sleeplessness occur
■ cough is accompanied by rash or persistent headache
■ symptoms are accompanied by fever

PREGNANCY OR BREAST FEEDING

If pregnant or breast-feeding, ask a health professional before use.

Keep out of reach of children. In case of overdose, get medical help or contact a Poison Control Center right away.

Directions
adults and children 12 years of age and over: take 2 tablets every 6 to 8 hours, not to exceed 8 tablets in 24 hours, or as directed by a doctor
children 6 to under 12 years of age: take 1 tablet every 6 to 8 hours, not to exceed 4 tablets in 24 hours, or as directed by a doctor
children under 6 years of age: ask a doctor

Other information
■ each tablet contains calcium 30 mg
■ keep container tightly closed
■ protect from light

Inactive ingredients
ammonium hydroxide, anhydrous dibasic calcium phosphate, calcium carbonate, carmellose, carnauba wax, croscarmellose sodium, dewaxed orange shellac, , FDandC Yellow No. 6 aluminum lake as color additive, glycyrrhiza extract, hydroxypropyl cellulose, hypromellose, lactose monohydrate, magnesium stearate, microcrystalline cellulose, partially hydrolyzed polyvinyl alcohol, polyethylene glycol 6000, propylene glycol, silicon dioxide, simethicone, sugar, talc, titanium dioxide